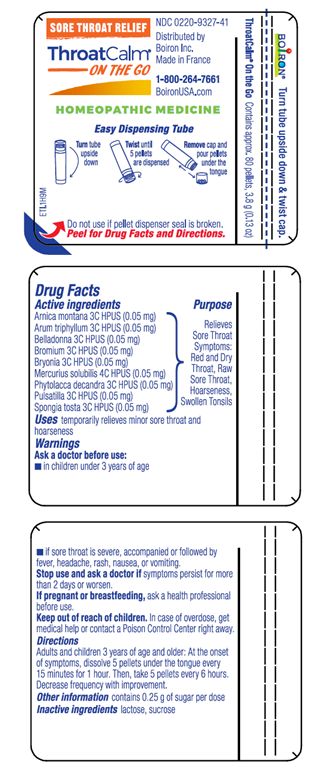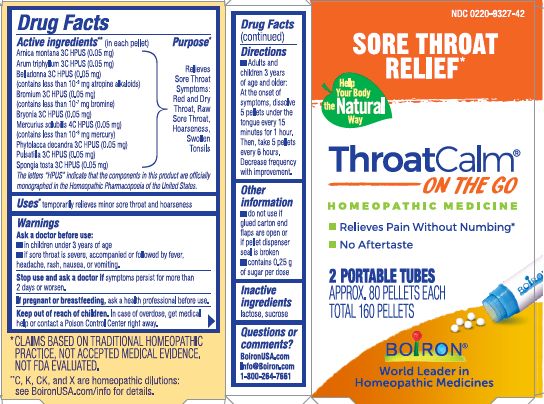 DRUG LABEL: THROATCALM
NDC: 0220-9327 | Form: PELLET
Manufacturer: Boiron
Category: homeopathic | Type: HUMAN OTC DRUG LABEL
Date: 20230131

ACTIVE INGREDIENTS: ARISAEMA TRIPHYLLUM ROOT 3 [hp_C]/1 1; ATROPA BELLADONNA 3 [hp_C]/1 1; MERCURIUS SOLUBILIS 4 [hp_C]/1 1; BROMINE 3 [hp_C]/1 1; BRYONIA ALBA ROOT 3 [hp_C]/1 1; SPONGIA OFFICINALIS SKELETON, ROASTED 3 [hp_C]/1 1; PHYTOLACCA AMERICANA ROOT 3 [hp_C]/1 1; PULSATILLA VULGARIS 3 [hp_C]/1 1; ARNICA MONTANA 3 [hp_C]/1 1
INACTIVE INGREDIENTS: LACTOSE, UNSPECIFIED FORM; SUCROSE

ThroatCalm Pellets

Active ingredient** (in each pellet)

Arnica montana 3C HPUS (0.05 mg)

Arum triphyllum 3C HPUS (0.05 mg)

Belladonna 3C HPUS (0.05 mg) (contains less than 10-9 mg atropine alkaloids)

Bromium 3C HPUS (0.05 mg) (contains less than 10-7 mg bromine)

Bryonia 3C HPUS (0.05 mg)

Mercurius solubilis 4C HPUS (0.05 mg) (contains less than 10-9 mg mercury)

Phytolacca decandra 3C HPUS (0.05 mg)

Pulsatilla 3C HPUS (0.05 mg)

Spongia tosta 3C HPUS (0.05 mg)

The letters "HPUS" indicate that the components in the product are officially monographed in the Homeopathic Pharmacopoeia on the United States.

Purpose*

Relieves Sore Throat Symptoms: Red and Dry Throat, Raw Sore Throat, Hoarseness, Swollen Tonsils

Uses*

temporarily relieves minor sore throat and hoarseness

Ask a doctor before use:

- in children under 3 years of age
- if sore throat is severe, accompanied or followed by fever, headache, rash, nausea, or vomiting.

Stop use and ask a doctor if symptoms persist for more than 2 days or worsen.

PREGNANCY OR BREAST FEEDING

If pregnant or breastfeeding, ask a health professional before use.

Keep out of reach of children. In case of overdose, get medical help or contact a Poison Control Center right away.

DOSAGE AND ADMINISTRATION

- Adults and children 3 years of age and older: At the onset of symptoms, dissolve 5 pellets under the tongue every 15 minutes for 1 hour. Then, take 5 pellets every 6 hours. Decrease frequency with improvement.

INACTIVE INGREDIENT

lactose, sucrose

- do not use if glued carton end flaps are open or if pellet dispenser seal is broken
- contains 0.25 g of sugar per dose

Sore Throat Relief*

Relieves Pain Without Numbing*

No Aftertaste

2 PORTABLE TUBES

APPROX. 80 PELLETS EACH

TOTAL 160 PELLETS

Contains approx. 80 pellets, 3.8 g (0.13 oz)

Turn tube upside down

Twist until 5 pellets are dispensed

Remove cap and pour pellets under the tongue

Do not use if pellet dispenser seal is broken,

*CLAIMS BASED ON TRADITIONAL HOMEOPATHIC PRACTICE NOT ACCEPTED MEDICAL EVIDENCE. NOT FDA EVALUATED.
**C,K,CK, and X are homeopathic dilutions: see BoironUSA.com/info for details.

QUESTIONS

BoironUSA.com

Info@Boiron.com

1-800-264-7661

Made in France

Distributed by

Boiron Inc.

Newtown Square, PA 19073